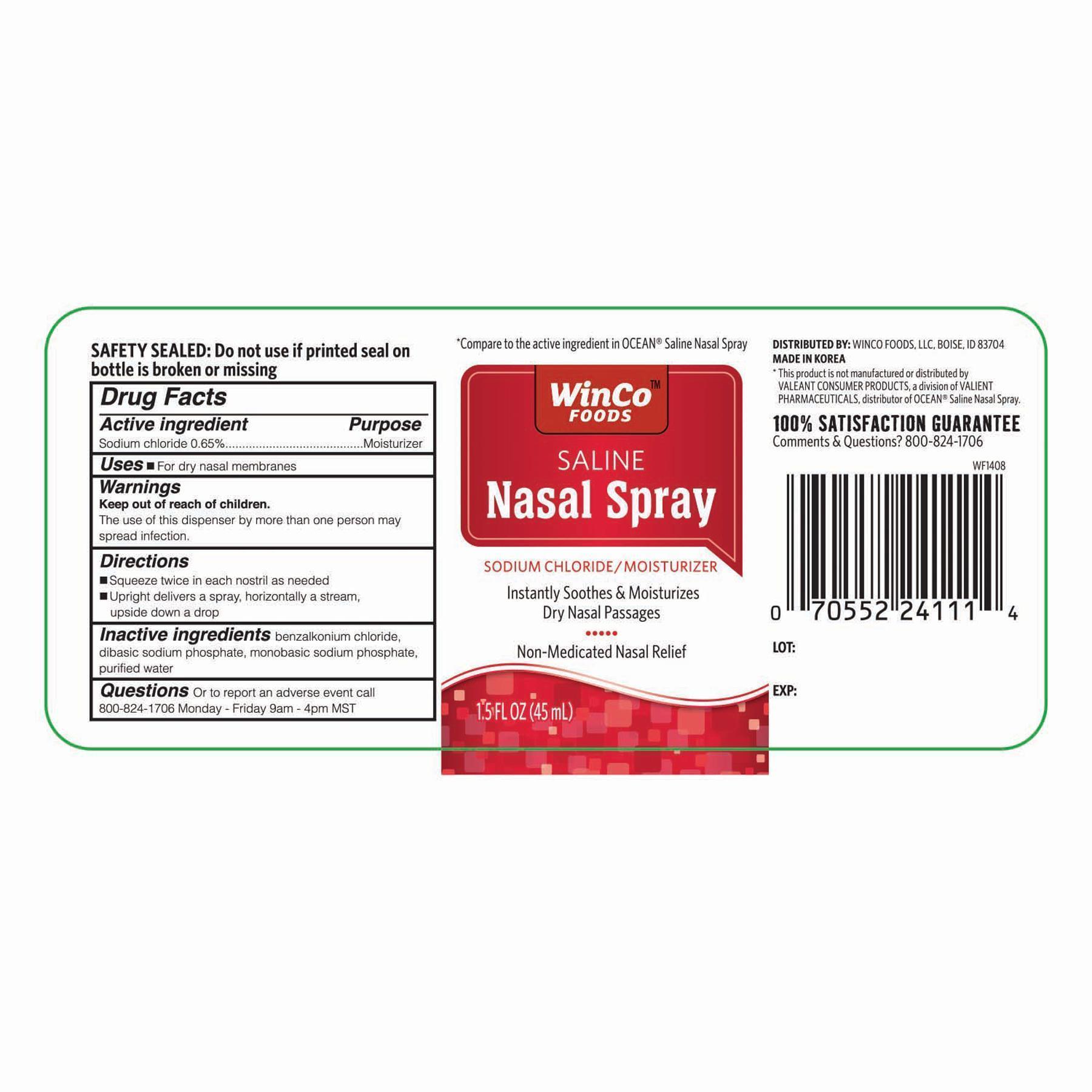 DRUG LABEL: WinCo Foods Saline Nasal
NDC: 67091-194 | Form: SPRAY
Manufacturer: WinCo Foods, LLC
Category: otc | Type: HUMAN OTC DRUG LABEL
Date: 20141126

ACTIVE INGREDIENTS: SODIUM CHLORIDE .65 g/100 mL
INACTIVE INGREDIENTS: BENZALKONIUM CHLORIDE; SODIUM PHOSPHATE, DIBASIC; WATER; SODIUM PHOSPHATE, MONOBASIC

Active Ingredient Purpose

Sodium chloride 0.65%----------------------------------------------------------------------- Moisturizer

Uses

- For dry nasal membranes

Warnings

keep out of reach of children

The use of this dispenser by more than one person may spread infections

Warnings

keep out of reach of children

The use of this dispenser by more than one person may spread infections

INDICATIONS AND USAGE

Direction

- Squeeze wtice in each nostril as needed
- Uprifht delivers a spray, horizontally a stream, upside down a drop

Inactive ingredients

benzalkonium chloride, dibasic sodium phosphate, monobasic sodium phosphate, purified water

DOSAGE AND ADMINISTRATION

DISTRIBUTED BY:

WINCO FODDS, LLC,

BOISE, ID 83704

MADE IN KOREA